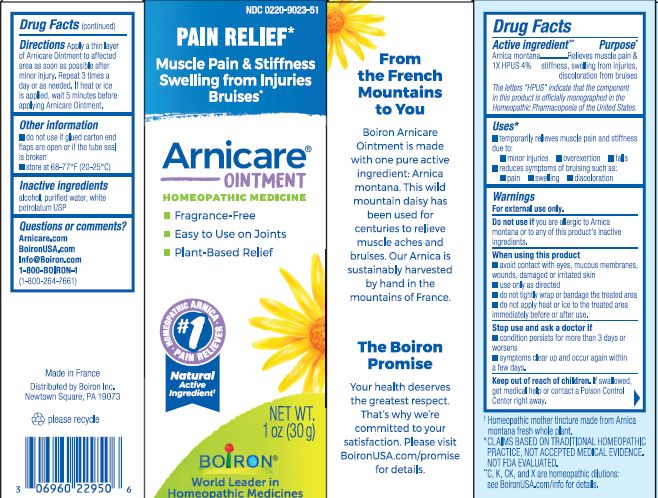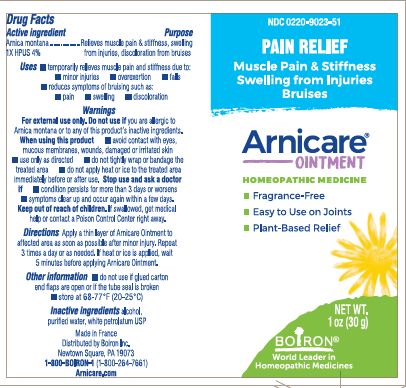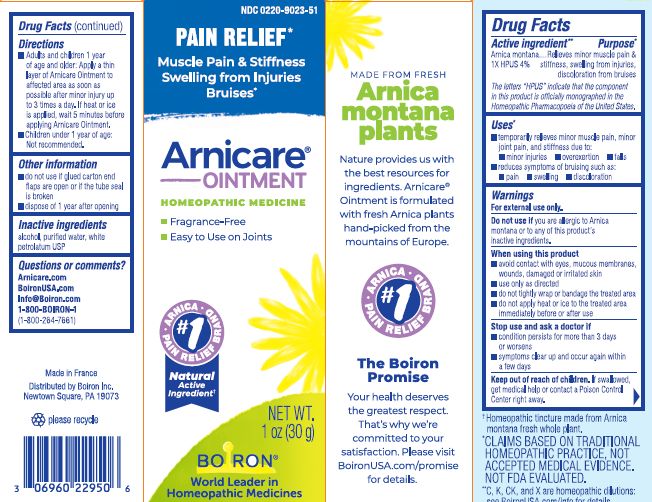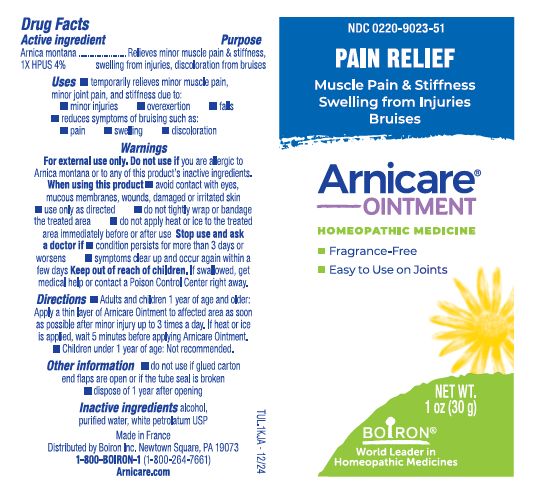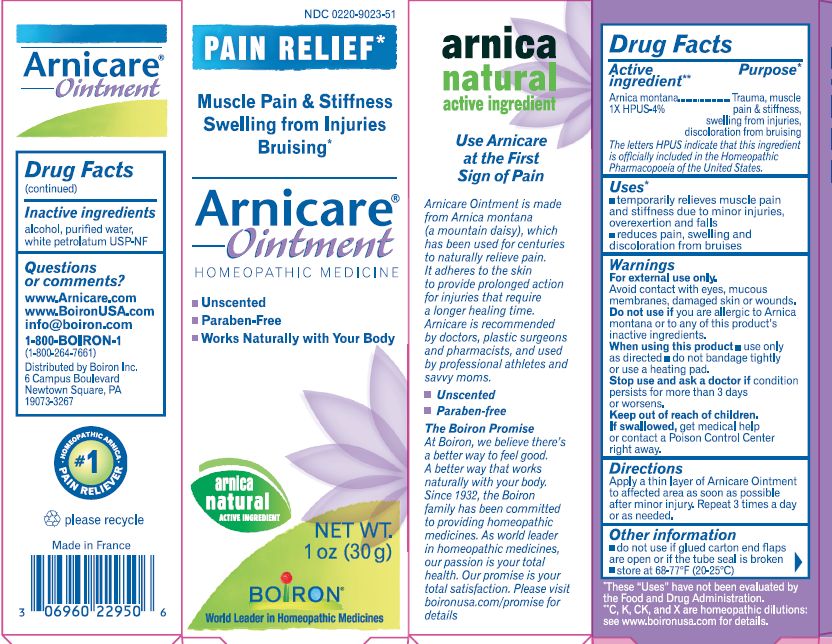 DRUG LABEL: Arnicare
NDC: 0220-9023 | Form: OINTMENT
Manufacturer: Laboratoires Boiron
Category: homeopathic | Type: HUMAN OTC DRUG LABEL
Date: 20241223

ACTIVE INGREDIENTS: ARNICA MONTANA 1 [hp_X]/1 g
INACTIVE INGREDIENTS: ALCOHOL; WATER; PETROLATUM

Arnicare Ointment

Active ingredients**

Arnica montana 1X HPUS 4%

The letters "HPUS" indicate that the component in this product is officially monographed in the Homeopathic Pharmacopoeia of the United States.

Purpose*

Arnica montana 1X HPUS 4% ... Relieves minor muscle pain & stiffness, swelling from injuries, discoloration from bruises

Uses*

- temporarily relieves minor muscle pain, minor joint pain, and stiffness due to:
- minor injuries
- overexertion
- falls
- reduces symptoms of bruising such as:
- pain
- swelling
- discoloration

WARNINGS

For external use only.

Do not use if you are allergic to Arnica montana or to any of this product's inactive ingredients.

WHEN USING

- avoid contact with eyes, mucous membranes, wounds, damaged or irritated skin
- use only as directed
- do not tightly wrap or bandage the treated area
- do not apply heat or ice to the treated area immediately before or after use

Stop use and ask doctor if

- condition persists for more than 3 days or worsens
- symptoms clear up and occur again within a few days

Keep out of reach of children. In case of accidental overdose, get medical help or contact a Poison Control Center right away.

DOSAGE AND ADMINISTRATION

- Adults and children 1 year of age and older: Apply a thin layer of Arnicare Ointment to affected area as soon as possible after minor injury up to 3 times a day. If heat or ice is applied, wait 5 minutes before applying Arnicare Ointment.
- Children under 1 year of age: Not recommended.

INACTIVE INGREDIENT

alcohol, purified water, white petrolatum USP

Questions, Comments?

Arnicare.com
Boironusa.com

Info@boironusa.com

1-800-BOIRON-1
(1-800-264-7661)
Distributed by Boiron Inc.
Newtown Square, PA 19073-3267

do not use if glued carton end flaps are open or if the tube seal is broken

dispose of 1 year after opening

1 oz (30g)

Pain Relief*

Muscle Pain & Stiffness Swelling from Injuries Bruises*

ɨ Homeopathic tincture made from Arnica montana fresh whole plant.

*CLAIMS BASED ON TRADITIONAL HOMEOPATHIC PRACTICE NOT ACCEPTED MEDICAL EVIDENCE. NOT FDA EVALUATED.
*C,K,CK, and X are homeopathic dilutions: see BoironUSA.com/info for details.

The letters "HPUS" indicate that the components in this product are officially monographed in the Homeopathic Pharmacopoeia of the United States.